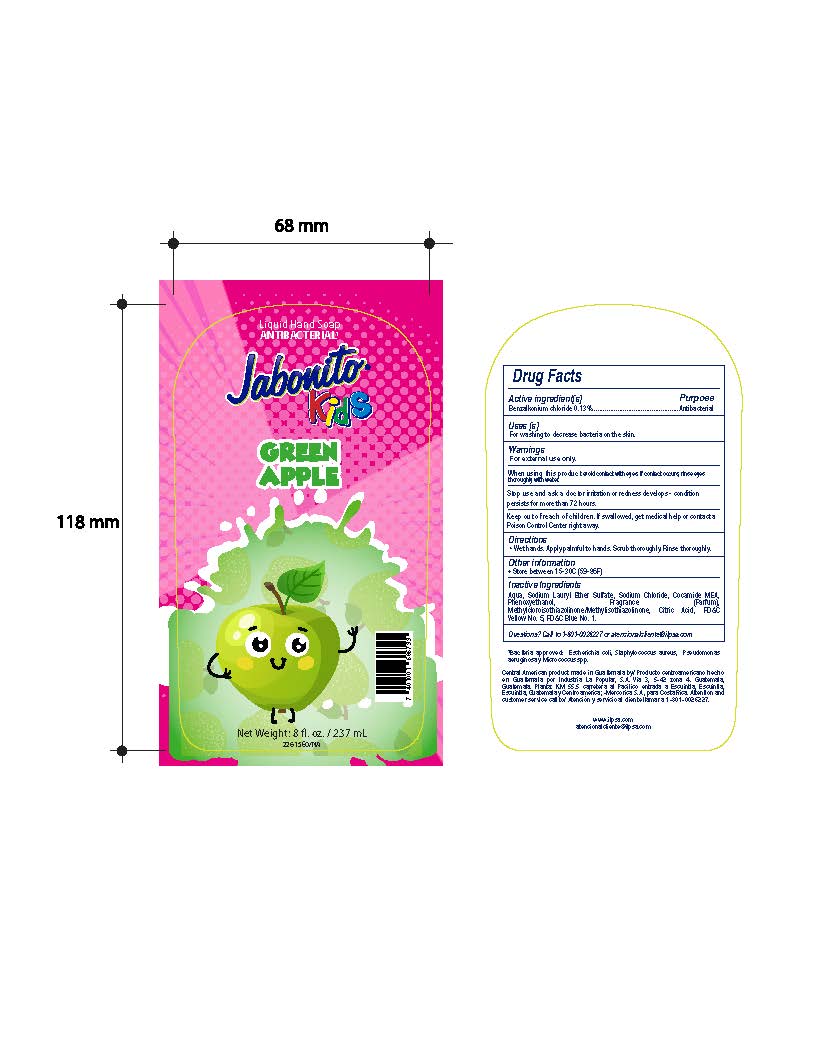 DRUG LABEL: Jabonito Kids Green Apple Liquid
NDC: 62476-009 | Form: LIQUID
Manufacturer: Industria La Popular, S.A.
Category: otc | Type: HUMAN OTC DRUG LABEL
Date: 20241202

ACTIVE INGREDIENTS: BENZALKONIUM CHLORIDE 0.31 g/237 mL
INACTIVE INGREDIENTS: ANHYDROUS CITRIC ACID; SODIUM LAURYL ETHOXYSULFATE; SODIUM CHLORIDE; METHYLCHLOROISOTHIAZOLINONE; COCO MONOETHANOLAMIDE; FD&C BLUE NO. 1; FD&C YELLOW NO. 5; METHYLISOTHIAZOLINONE; PHENOXYETHANOL; WATER

Jabonito Kids Green Apple Liquid Hand Soap

Active Ingredient

Benzalkonium Chloride 0.13%

Purpose

Antibacterial

Uses

For washing to decrease bacteria on the skin

Warnings

For External Use only.

When using this product

avoid contact with eyes. If contact occurs, rinse eyes thoroughly with water.

Stop use and ask a doctor

irritation or redness develops - condition persists for more than 72 hours.

Keep out of reach of children.

If swallowed, get medical help or contact a Poison Control Center right away

Directions

Wet hands. Apply palmful to hands. Scrub thoroughly. Rinse thoroughly.

Other Information

Store between 15-30C (59-86F)

Inactive Ingredients

Aqua, Sodium Lauryl Ether Sulfate, Sodium Chloride, Cocamide MEA, Phenoxyethanol, Fragrance (Parfum), Methylchloroisothiazolinone/Methylisothiazolinone, Citric Acid, FD&C Yellow No. 5, FD&C Blue No. 1.